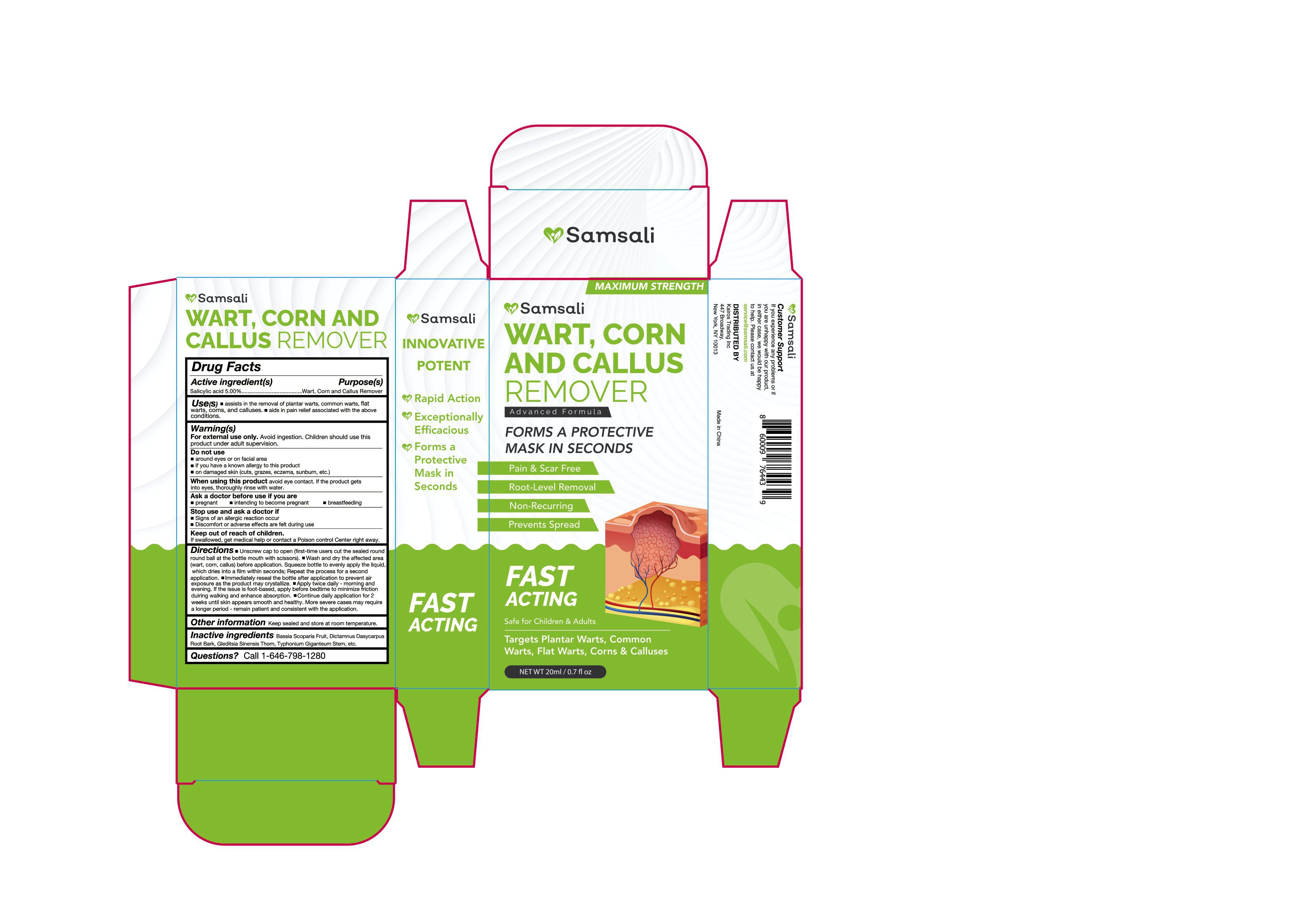 DRUG LABEL: Samsali Wart Remover
NDC: 83818-002 | Form: LIQUID
Manufacturer: Shenzhen Xinxin Yunhai Technology Co., Ltd.
Category: otc | Type: HUMAN OTC DRUG LABEL
Date: 20240118

ACTIVE INGREDIENTS: SALICYLIC ACID 5 g/100 mL
INACTIVE INGREDIENTS: BASSIA SCOPARIA FRUIT; TYPHONIUM GIGANTEUM STEM; DICTAMNUS DASYCARPUS ROOT BARK; GLEDITSIA SINENSIS THORN

83818-002

Active Ingredient

Salicylic acid 5.00%

Purpose

Wart, Corn and Callus Remover

Use

the removal of plantar warts, common warts, flat warts, corns, and calluses

Warnings

For external use only. Avoid ingestion. Children should use this
product under adult supervision.

Do not use

around eyes or on facial area if you have a known allergy to this product on damaged skin

When Using

avoid eye contact. If the product gets into eyes, thoroughly rinse with water.

Stop Use

Signs of an allergic reaction occur Discomfort or adverse effects are felt during use

Ask Doctor

pregnant, intending to become pregnant, breastfeeding

Keep Oot Of Reach Of Children

If swallowed, get medical help or contact a Poison control Center right away.

Directions

1. Unscrew cap to open (first-time users cut thesealed round round ball at the bottle mouth with scissors).

2. Wash and dry the affected area (wart, corn, callus) before application. Squeeze bottle to evenly apply the liquid,
which dries into a film within seconds; Repeat the process for a second application.

3. Immediately reseal the bottle after application to prevent air exposure as theproduct may crystallize.

4. Apply twice daily - morning and evening. Ifthe issue is foot-based, apply before bedtime to minimize friction duiring walking and enhance absorption.

5. Continue daily application for2 weeks until skin appears smooth and healthy. More severe cases may require a longer period - remain patient and consistent with the application.

Other information

Keep sealed and store at room temperature.

Inactive ingredients

Bassia Scoparia Fruit, Dictamnus Dasycarpus Root Bark, Gleditsia Sinensis Thorn, Typhonium Giganteum Stem

Questions

Call 1-646-798-1280